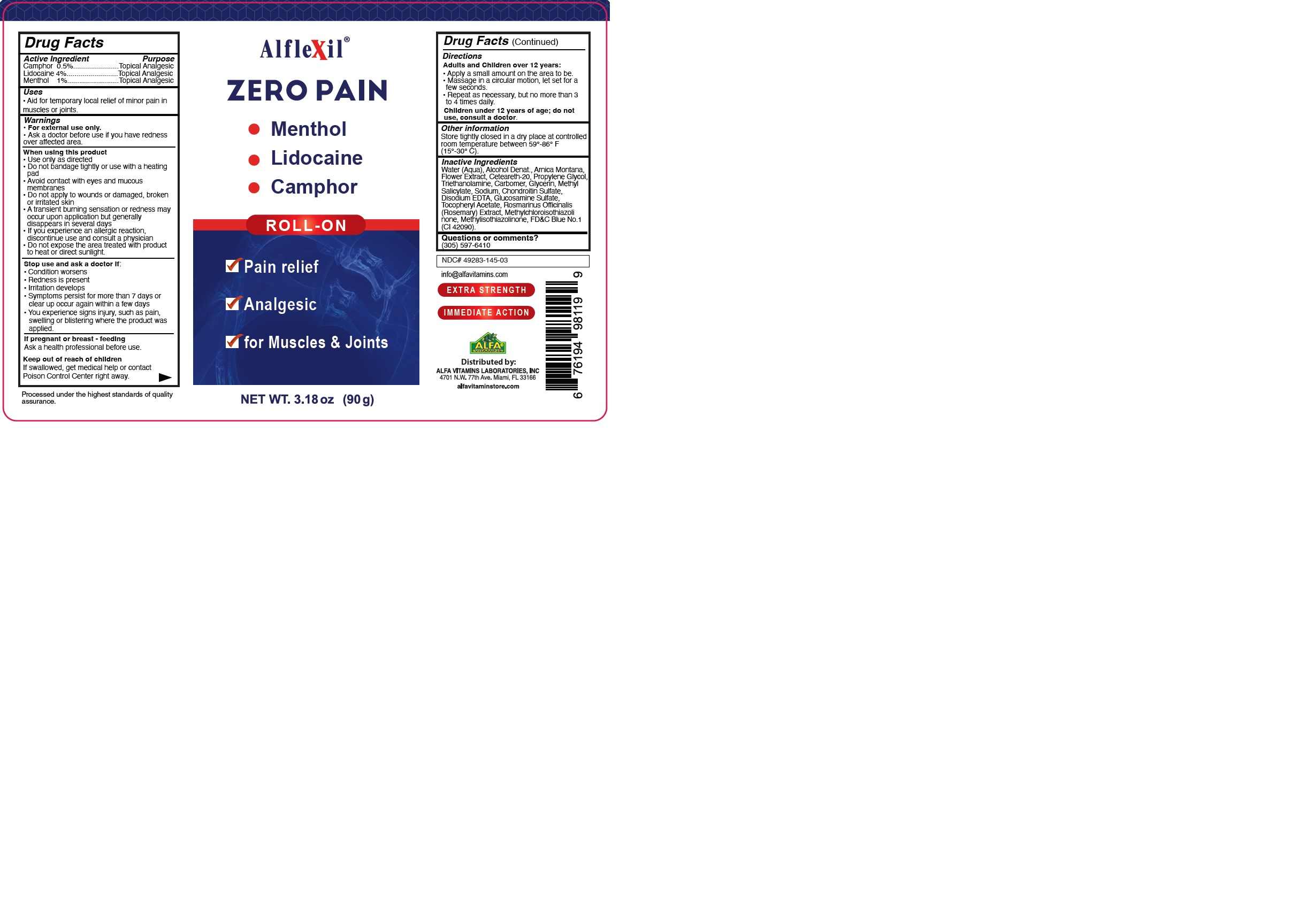 DRUG LABEL: ALFLEXIL ZERO PAIN
NDC: 49283-145 | Form: GEL
Manufacturer: CHEMCO CORPORATION
Category: otc | Type: HUMAN OTC DRUG LABEL
Date: 20230914

ACTIVE INGREDIENTS: LIDOCAINE HYDROCHLORIDE 4 g/100 g; CAMPHOR (SYNTHETIC) 0.5 g/100 g; MENTHOL 1 g/100 g
INACTIVE INGREDIENTS: EDETATE DISODIUM ANHYDROUS; WATER; ALCOHOL; CARBOMER 940; METHYLISOTHIAZOLINONE; METHYL SALICYLATE; FD&C BLUE NO. 1; GLYCERIN; SODIUM CHONDROITIN SULFATE (PORCINE; 5500 MW); GLUCOSAMINE SULFATE; ROSMARINUS OFFICINALIS FLOWERING TOP; METHYLCHLOROISOTHIAZOLINONE; ARNICA MONTANA FLOWER WATER; POLYOXYL 20 CETOSTEARYL ETHER; PROPYLENE GLYCOL; TROLAMINE; .ALPHA.-TOCOPHEROL ACETATE

49283-145-03

ACTIVE INGREDIENT

Camphor 0.5%

Lidocaine 4%

Menthol 1%

PURPOSE

Topical Analgesic

Use

Aid for temporary local relief of minor pain in muscles or joints.

WARNINGS

For external use only. · Ask a doctor before use if you have redness over affected area.

WHEN USING

Use only as directed
Do not bandage tightly or use with a heating pad.
Avoid contact with eyes and mucous membranes.
Do not apply to wounds or damaged, broken or irritated skin.
A transient burning sensation or redness may occur upon application but generally disappears in several days.
Do not use in large quantities, particularly over raw surfaces or blistered areas.
If you experience an allergic reaction, discontinue use and consult a physician.

Do not expose the area treated with product to heat or direct sunlight.

STOP USE

Condition worsens.
Redness is present.
Irritation develops.
Symptoms persist for more than 7 days or clear up occur again within a few days.

You experience signs injury, such as pain, swelling or blistering where the product was applied.

If pregnant or breast – feeding

Ask a health professional before use.

KEEP OUT OF REACH OF CHILDREN

If swallowed, get medical help or contact a Poison Control Center right away.

Directions

Adults and Children over 12 years of age:

Apply a small amount on the area to be.
Massaged in a circular motion, let set for a few seconds.
Repeat as necessary, but no more than 3 to 4 times daily.

Children under 12 years of age; do not use, consult a doctor.

Other information

Store tightly closed in a dry place at controlled room temperature between 59°-86° F (15°-30° C).

INACTIVE INGREDIENT

Water (Aqua), Alcohol Denat, Arnica Montana Flower Extract, Ceteareth-20, Propylene Glycol, Triethanolamine, Carbomer, Glycerin, Methyl Salicylate, Sodium Chondroitin Sulfate, Disodium EDTA, Glucosamine Sulfate, Tocopheryl Acetate, Rosmarinus Officinalis (Rosemary) Extract, Methylchloroisothiazolinone, Methylisothiazolinone, FD&C Blue No.1 (CI 42090).

QUESTIONS

+1(305)597-6410